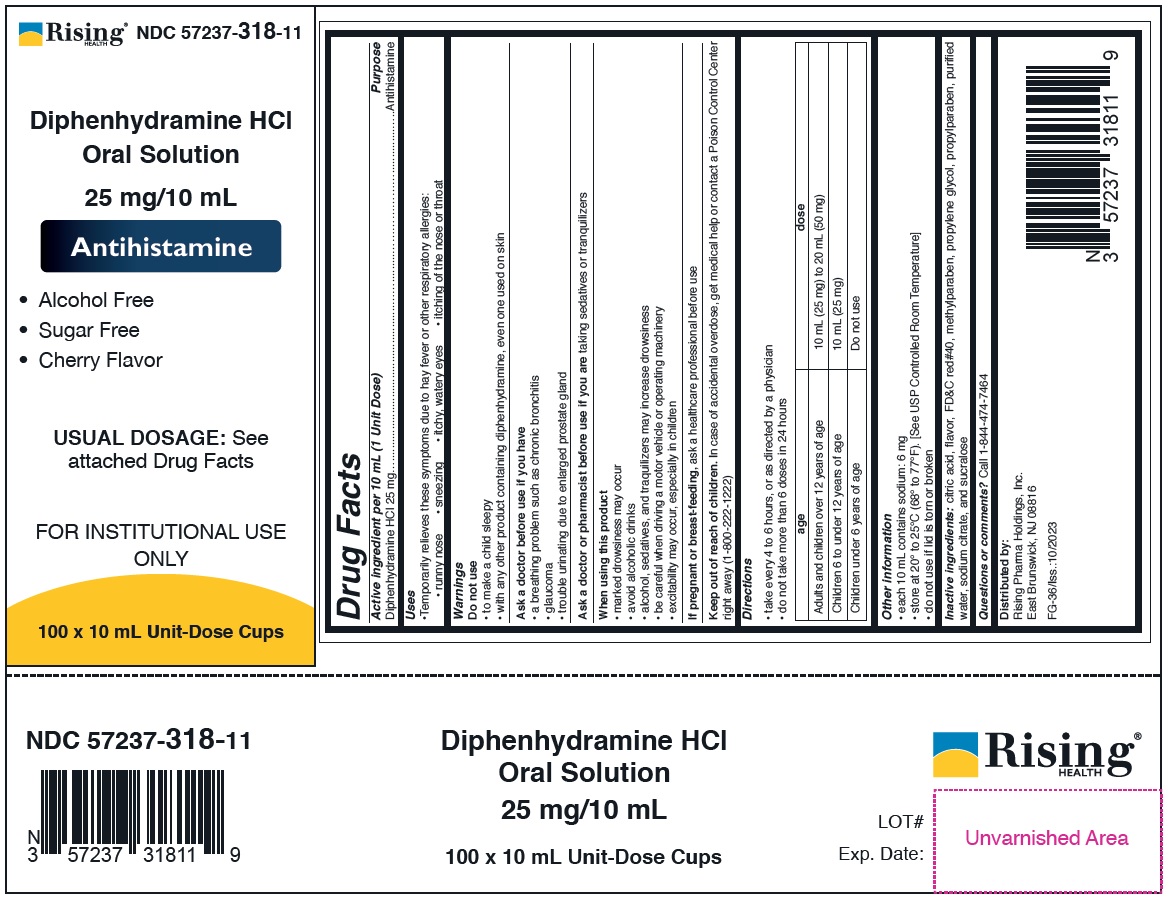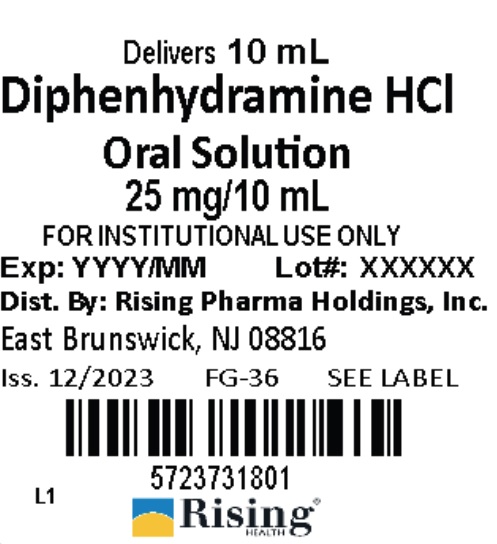 DRUG LABEL: Diphenhydramine HCl Oral Solution
NDC: 57237-318 | Form: SOLUTION
Manufacturer: Rising Pharma Holdings, Inc.
Category: otc | Type: HUMAN OTC DRUG LABEL
Date: 20250701

ACTIVE INGREDIENTS: DIPHENHYDRAMINE HYDROCHLORIDE 25 mg/10 mL
INACTIVE INGREDIENTS: CITRIC ACID MONOHYDRATE; FD&C RED NO. 40; METHYLPARABEN; PROPYLENE GLYCOL; PROPYLPARABEN; SODIUM CITRATE; SUCRALOSE; WATER

Diphenhydramine HCl Oral Solution 25 mg/10 mL

Drug Facts

Active ingredient per 10 mL (1 Unit Dose)

Diphenhydramine HCl 25 mg

Purpose

Antihistamine

Uses

• Temporarily relieves these symptoms due to hay fever or other respiratory allergies:

• runny nose • sneezing • itchy, watery eyes • itching of the nose or throat

Warnings

Do not use

• to make a child sleepy
• with any other product containing diphenhydramine, even one used on skin

Ask a doctor before use if you have

• a breathing problem such as chronic bronchitis
• glaucoma
• trouble urinating due to enlarged prostate gland

Ask a doctor or pharmacist before use if you are taking sedatives or tranquilizers

When using this product

• marked drowsiness may occur
• avoid alcoholic drinks
• alcohol, sedatives, and traquilizers may increase drowsiness
• be careful when driving a motor vehicle or operating machinery
• excitability may occur, especially in children

If pregnant or breast-feeding, ask a healthcare professional before use

Keep out of reach of children. In case of accidental overdose, get medical help or contact a Poison Control Center right away (1-800-222-1222)

Directions

• take every 4 to 6 hours, or as directed by a physician
• do not take more than 6 doses in 24 hours

age | dose
Adults and children over 12 years of age | 10 mL (25 mg) to 20 mL (50 mg)
Children 6 to under 12 years of age | 10 mL (25 mg)
Children under 6 years of age | Do not use

Other information

• each 10 mL contains sodium: 6 mg
• store at 20° to 25°C (68° to 77°F). [See USP Controlled Room Temperature]
• do not use if lid is torn or broken

INACTIVE INGREDIENT

Inactive ingredients: citric acid, flavor, FD&C red#40, methylparaben, propylene glycol, propylparaben, purified water, sodium citrate, and sucralose

Questions or comments? Call 1-844-474-7464

Distributed by:
Rising Pharma Holdings, Inc.
East Brunswick, NJ 08816

FG-36/Iss.:10/2023

NDC Information -

25 mg/10 mL

Each 10 mL of Diphenhydramine HCl Oral Solution contains Diphenhydramine HCl 25 mg and is supplied in the following oral dosage forms:

NDC 57237-318-01: 10 mL unit dose cup

NDC 57237-318-11: 100 x 10 mL Unit-Dose Cups

PRINCIPAL DISPLAY PANEL

25 mg/10 mL

Case Label NDC 57237-318-11

Lid Label NDC 57237-318-01